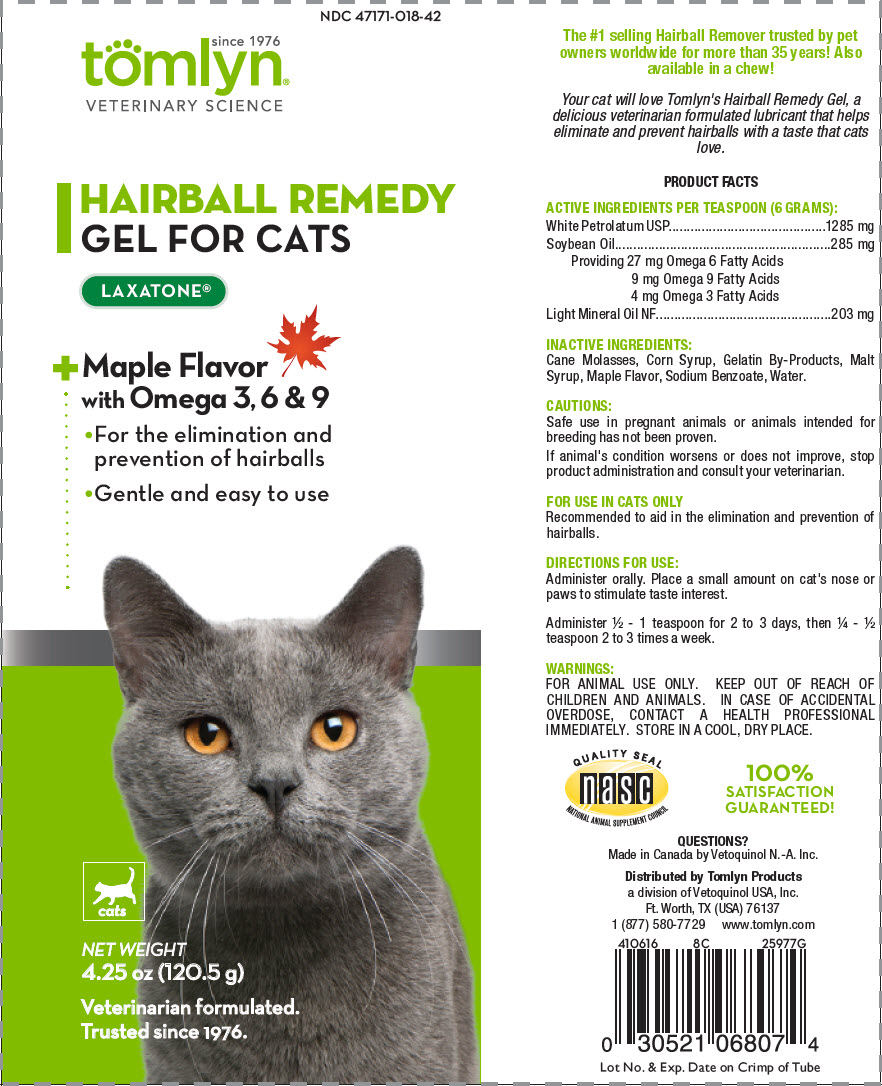 DRUG LABEL: Laxatone
NDC: 47171-018 | Form: GEL
Manufacturer: Tomlyn Products, a Divison of Vetoquinol USA, Inc.
Category: animal | Type: OTC ANIMAL DRUG LABEL
Date: 20200131

ACTIVE INGREDIENTS: Petrolatum 214.2 mg/1 g; Mineral Oil 33.8 mg/1 g; Soybean Oil 47.5 mg/1 g
INACTIVE INGREDIENTS: Water; Corn Syrup; Maltose Syrup; Molasses; GELATIN, UNSPECIFIED; Sodium Benzoate

Laxatone®

The #1 selling Hairball Remover trusted by pet owners worldwide for more than 35 years! Also available in a chew!

VETERINARY INDICATIONS

Your cat will love Tomlyn's Hairball Remedy Gel, a delicious veterinarian formulated lubricant that helps eliminate and prevent hairballs with a taste that cats love.

PRODUCT FACTS

DESCRIPTION

ACTIVE INGREDIENTS PER TEASPOON (6 GRAMS):

White Petrolatum USP | 1285 mg
Soybean Oil | 285 mg
Providing 27 mg Omega 6 Fatty Acids 9 mg Omega 9 Fatty Acids 4 mg Omega 3 Fatty Acids
Light Mineral Oil NF | 203 mg

INACTIVE INGREDIENTS:

Cane Molasses, Corn Syrup, Gelatin By-Products, Malt Syrup, Maple Flavor, Sodium Benzoate, Water.

SAFE HANDLING WARNING

CAUTIONS:

Safe use in pregnant animals or animals intended for breeding has not been proven.

If animal's condition worsens or does not improve, stop product administration and consult your veterinarian.

FOR USE IN CATS ONLY

Recommended to aid in the elimination and prevention of hairballs.

DOSAGE AND ADMINISTRATION

DIRECTIONS FOR USE:

Administer orally. Place a small amount on cat's nose or paws to stimulate taste interest.

Administer ½ - 1 teaspoon for 2 to 3 days, then ¼ - ½ teaspoon 2 to 3 times a week.

WARNINGS:

FOR ANIMAL USE ONLY. KEEP OUT OF REACH OF CHILDREN AND ANIMALS. IN CASE OF ACCIDENTAL OVERDOSE, CONTACT A HEALTH PROFESSIONAL IMMEDIATELY. STORE IN A COOL, DRY PLACE.

QUALITY SEAL
NATIONAL ANIMAL SUPPLEMENT COUNCIL

100%
SATISFACTION
GUARANTEED!

QUESTIONS?
Made in Canada by Vetoquinol N.-A. Inc.

Distributed by Tomlyn Products
a division of Vetoquinol USA, Inc.
Ft. Worth, TX (USA) 76137
1 (877) 580-7729
www.tomlyn.com

410616
8C
25977G

Lot No. & Exp. Date on Crimp of Tube

PRINCIPAL DISPLAY PANEL - 120.5 g Tube Label

NDC 47171-018-42

since 1976
tomlyn®
VETERINARY SCIENCE

HAIRBALL REMEDY
GEL FOR CATS

LAXATONE®

+Maple Flavor
with Omega 3, 6 & 9

- For the elimination and
  prevention of hairballs
- Gentle and easy to use

cats

NET WEIGHT
4.25 oz (120.5 g)

Veterinarian formulated.
Trusted since 1976.